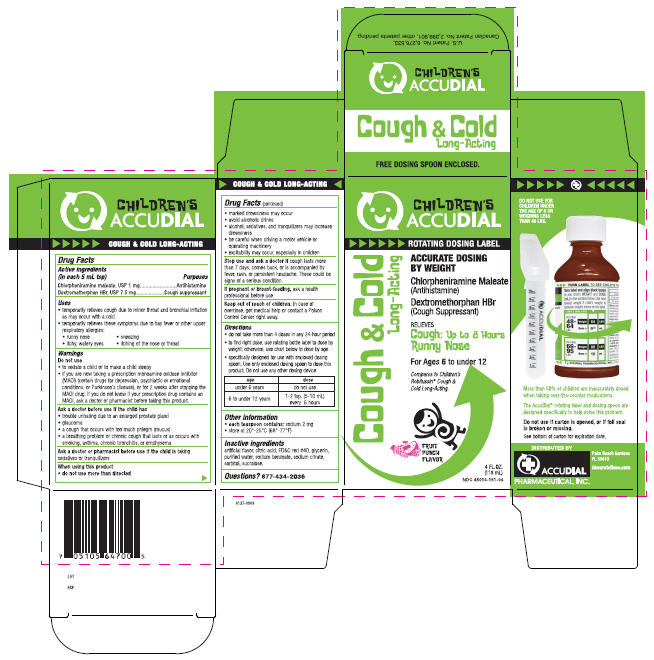 DRUG LABEL: Cough and Cold
NDC: 45014-151 | Form: LIQUID
Manufacturer: Accudial Pharmaceutical, Inc.
Category: otc | Type: HUMAN OTC DRUG LABEL
Date: 20091111

ACTIVE INGREDIENTS: Chlorpheniramine Maleate 1 mg/5 mL; Dextromethorphan Hydrobromide 7.5 mg/5 mL
INACTIVE INGREDIENTS: Fruit; Citric Acid Monohydrate; FD&C RED NO. 40; Glycerin; Water; Sodium Benzoate; Sodium Citrate; Sorbitol; Sucralose

Children's
ACCUDIAL

COUGH & COLD LONG-ACTING

Drug Facts

ACTIVE INGREDIENT

PURPOSE

Active ingredients (in each 5 mL tsp) | Purposes
Chlorpheniramine maleate, USP 1 mg | Antihistamine
Dextromethorphan HBr, USP 7.5 mg | Cough suppressant

Uses

- temporarily relieves cough due to minor throat and bronchial irritation as may occur with a cold
- temporarily relieves these symptoms due to hay fever or other upper respiratory allergies:
  - runny nose
  - sneezing
  - itchy, watery eyes
  - itching of the nose or throat

Warnings

Do not use

- to sedate a child or to make a child sleepy
- if you are now taking a prescription monoamine oxidase inhibitor (MAOI) (certain drugs for depression, psychiatric or emotional conditions, or Parkinson's disease), or for 2 weeks after stopping the MAOI drug. If you do not know if your prescription drug contains an MAOI, ask a doctor or pharmacist before taking this product.

Ask a doctor before use if the child has

- trouble urinating due to an enlarged prostate gland
- glaucoma
- a cough that occurs with too much phlegm (mucus)
- a breathing problem or chronic cough that lasts or as occurs with smoking, asthma, chronic bronchitis, or emphysema

Ask a doctor or pharmacist before use if the child is taking sedatives or tranquilizers

When using this product

- do not use more than directed
- marked drowsiness may occur
- avoid alcoholic drinks
- alcohol, sedatives, and tranquilizers may increase drowsiness
- be careful when driving a motor vehicle or operating machinery
- excitability may occur, especially in children

Stop use and ask a doctor if cough lasts more than 7 days, comes back, or is accompanied by fever, rash, or persistent headache. These could be signs of a serious condition.

PREGNANCY OR BREAST FEEDING

If pregnant or breast-feeding, ask a health professional before use.

Keep out of reach of children. In case of overdose, get medical help or contact a Poison Control Center right away.

Directions

- do not take more than 4 doses in any 24-hour period
- to find right dose, use rotating bottle label to dose by weight; otherwise, use chart below to dose by age
- specifically designed for use with enclosed dosing spoon. Use only enclosed dosing spoon to dose this product. Do not use any other dosing device

age | dose
under 6 years | do not use
6 to under 12 years | 1-2 tsp. (5-10 mL) every 6 hours

Other information

- each teaspoon contains: sodium 2 mg
- store at 20°-25°C (68°-77°F)

Inactive ingredients

artificial flavor, citric acid, FD&C red #40, glycerin, purified water, sodium benzoate, sodium citrate, sorbitol, sucralose.

Questions?

877-434-2036

PRINCIPAL DISPLAY PANEL - 118 mL Carton

CHILDREN'S
ACCUDIAL

ROTATING DOSING LABEL

Cough & Cold
Long-Acting

ACCURATE DOSING
BY WEIGHT

Chlorpheniramine Maleate
(Antihistamine)

Dextromethorphan HBr
(Cough Suppressant)

RELIEVES
Cough: Up to 8 Hours
Runny Nose

For Ages 6 to under 12

Compares to Children's
Robitussin® Cough &
Cold Long-Acting.

FRUIT
PUNCH
FLAVOR

4 FL. OZ.
(118 mL)
NDC 45014-151-04